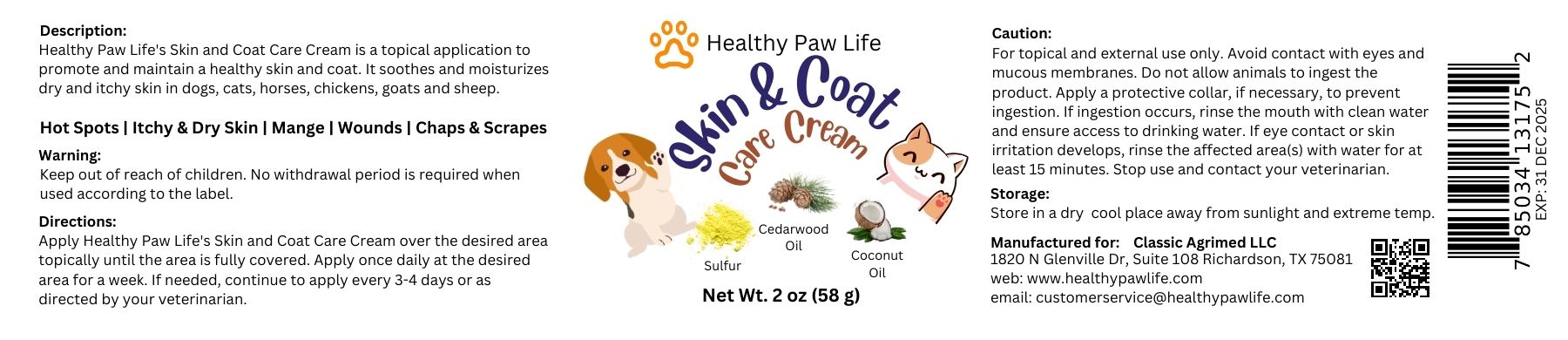 DRUG LABEL: HEALHY PAW LIFE SULFUR
NDC: 86130-903 | Form: CREAM
Manufacturer: CLASSIC AGRIMED LLC
Category: animal | Type: OTC ANIMAL DRUG LABEL
Date: 20231118

ACTIVE INGREDIENTS: SULFUR 10 g/100 g
INACTIVE INGREDIENTS: CEDAR LEAF OIL 0.2 g/100 g; COCONUT OIL 0.1 g/100 g

HEALTHY PAW LIFE SULFUR CREAM

Description:
Healthy Paw Life's Skin and Coat Care Cream is a topical application to promote and maintain a healthy skin and coat. It soothes and moisturizes dry and itchy skin in dogs, cats, horses, chickens, goats and sheep.

Hot Spots | Itchy & Dry Skin | Mange | Wounds | Chaps & Scrapes

Warning:
Keen out of reach of children. No withdrawal period is reauired when used according to the label

Storage:

Store in a dry cool place away from sunlight and extreme temp.

Directions.
Apply Healthy Paw Life's Skin and Coat Care Cream over the desired area topically until the area is fully covered. Apply once daily at the desired area for a week. If needed, continue to apply every 3-4 days or as directed by your veterinarian.

Caution:
For topical and external use only. Avoid contact with eyes and mucous membranes. Do not allow animals to ingest the product. Apply a protective collar, if necessary, to prevent ingestion. If ingestion occurs, rinse the mouth with clean water and ensure access to drinking water. If eye contact or skin irritation develops, rinse the affected area(s) with water for at least 15 minutes. Stop use and contact your veterinarian.